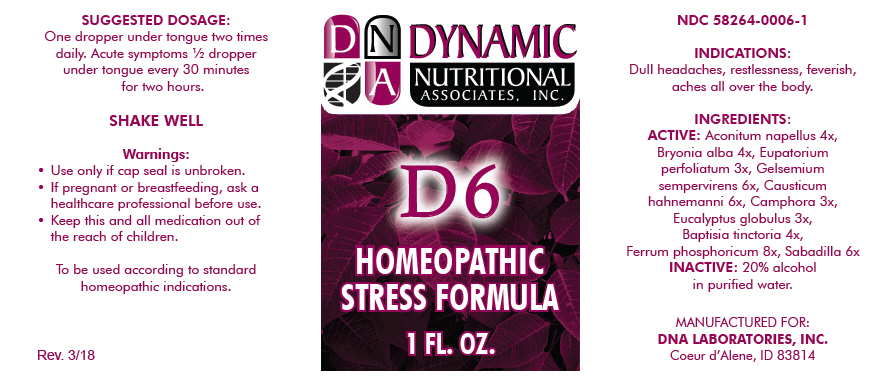 DRUG LABEL: D-6
NDC: 58264-0006 | Form: SOLUTION
Manufacturer: DNA Labs, Inc.
Category: homeopathic | Type: HUMAN OTC DRUG LABEL
Date: 20250113

ACTIVE INGREDIENTS: ACONITUM NAPELLUS 4 [hp_X]/1 mL; BRYONIA ALBA WHOLE 4 [hp_X]/1 mL; EUPATORIUM PERFOLIATUM FLOWERING TOP 3 [hp_X]/1 mL; GELSEMIUM SEMPERVIRENS ROOT 6 [hp_X]/1 mL; CAUSTICUM 6 [hp_X]/1 mL; CAMPHOR (NATURAL) 3 [hp_X]/1 mL; EUCALYPTUS GLOBULUS LEAF 3 [hp_X]/1 mL; BAPTISIA TINCTORIA 4 [hp_X]/1 mL; FERROSOFERRIC PHOSPHATE 8 [hp_X]/1 mL; SCHOENOCAULON OFFICINALE SEED 6 [hp_X]/1 mL
INACTIVE INGREDIENTS: ALCOHOL; WATER

D-6

NDC 58264-0006-1

INDICATIONS

PURPOSE

Dull headaches, restlessness, feverish, aches all over the body.

INGREDIENTS

ACTIVE

Aconitum napellus 4x, Bryonia alba 4x, Eupatorium perfoliatum 3x, Gelsemium sempervirens 6x, Causticum hahnemanni 6x, Camphora 3x, Eucalyptus globulus 3x, Baptisia tinctoria 4x, Ferrum phosphoricum 8x, Sabadilla 6x

INACTIVE

20% alcohol in purified water.

SUGGESTED DOSAGE

One dropper under tongue two times daily. Acute symptoms ½ dropper under tongue every 30 minutes for two hours.

STORAGE AND HANDLING

SHAKE WELL

Warnings

- Use only if cap seal is unbroken.

PREGNANCY OR BREAST FEEDING

- If pregnant or breastfeeding, ask a healthcare professional before use.

KEEP OUT OF REACH OF CHILDREN

- Keep this and all medication out of the reach of children.

To be used according to standard homeopathic indications.

PRINCIPAL DISPLAY PANEL - 1 FL. OZ. Bottle Label

DYNAMIC
NUTRITIONAL
ASSOCIATES, INC.

D 6

HOMEOPATHIC
STRESS FORMULA

1 FL. OZ.